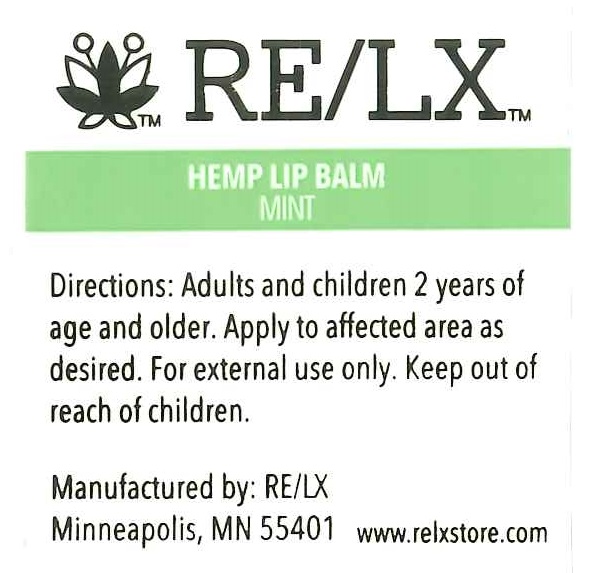 DRUG LABEL: HEMP LIP BALM
NDC: 73278-201 | Form: LIPSTICK
Manufacturer: Nemadji Management LLC
Category: otc | Type: HUMAN OTC DRUG LABEL
Date: 20190807

ACTIVE INGREDIENTS: OCTISALATE 7.3 g/100 mL; OXYBENZONE 0.4 g/100 mL
INACTIVE INGREDIENTS: CANNABIS SATIVA SUBSP. SATIVA FLOWERING TOP; COCONUT OIL; YELLOW WAX; PETROLATUM; CANDELILLA WAX; DIMETHICONE; ALOE VERA WHOLE; .ALPHA.-TOCOPHEROL ACETATE

ACTIVE INGREDIENTS

OCTISALATE 7.3%

OXYBENZONE 4.7%

PURPOSE

SUNSCREEN

WARNINGS

EXTERNAL USE ONLY

KEEP OUT OF REACH OF CHILDREN.

USES

PREVENTS SUNBURN

DIRECTIONS

APPLY TO AFFECTED AREA AS DESIRED.

INACTIVE INGREDIENTS

Hemp flower oil, Coconut oil, Beeswax, Patrolatum, Candelilla wax, Dimethicone, Aloe oil, Flavor, Tocopherol Acetate.